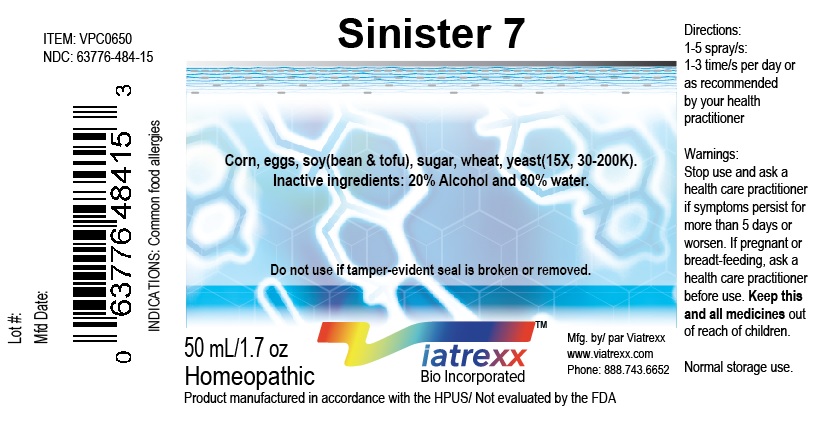 DRUG LABEL: Viatrexx- Sinister 7
NDC: 63776-484 | Form: SPRAY
Manufacturer: VIATREXX BIO INCORPORATED
Category: homeopathic | Type: HUMAN OTC DRUG LABEL
Date: 20190319

ACTIVE INGREDIENTS: Corn 30 [kp_C]/1 mL; Egg 30 [kp_C]/1 mL; Cow Milk 30 [kp_C]/1 mL; Soy Protein 30 [kp_C]/1 mL; Sucrose 30 [kp_C]/1 mL; Wheat 30 [kp_C]/1 mL; Yeast, Unspecified 30 [hp_X]/1 mL
INACTIVE INGREDIENTS: Water; Alcohol

Sinister 7

Active Ingredients

Corn (15X, 30K & 200K), Eggs (15X, 30K & 200K), Milk (15X, 30K & 200K), Soy (15X, 30K & 200K), Sugar (15X, 30K & 200K), Wheat (15X, 30K & 200K), Yeast (15X, 30K & 200K)

Purpose

Corn
Eggs
Milk
Soy
Sugar
Wheat
Yeast

Corn sensitivities
Egg sensitivities
Milk sensitivities
Soy sensitivities
Sugar sensitivities
Wheat sensitivities
Yeast sensitivities

Description

Viatrexx- Sinister 7 is a homeopathic product composed of physiological (low dose and low low dose) natural micro nutrients. These micro particles are designed to nourish the system.

Uses

For sensitivities to common foods.

Warnings

Stop use and ask a health care practitioner if symptoms persist for more than five days or worsen. If pregnant or breastfeeding, ask a health care practitioner before use.

Dosage

1-3 spray(s); 1-3 time(s) per day or as recommended by your health care practitioner.

Inactive Ingredients

20% Alcohol and 80% Water

Other Information

Product availability

Product may be acquired in 0.5, 30, 50, 100, 250 mL bottles.

References upon request

To report SUSPECTED ADVERSE REACTIONS, contact the FDA at 1-800-FDA-1088 or www.fda.gov/medwatch

Distributed by
Viatrexx Bio Incorporated
Newark, DE, USA, 19713

Manufactured by
8046255 Canada Inc
Beloeil, Qc, J3G 6S3
Date of last revision March 2019

For Questions and comments
Info@Viatrexx.com
www.Viatrexx.com

PACKAGE LABEL.PRINCIPAL DISPLAY PANEL

NDC: 63776-484-11
Item: VPC0650
Viatrexx Bio Incorporated
Viatrexx- Sinister 7
Box of 1 X 0.5 mL ampule
For Oral and Topical Use
Expiry date: Lot #:
Manufactured for:
Viatrexx Bio Incorporated Newark, DE, USA, 19713
www.Viatrexx.com
Ingredients, homeopathic
See insert or www.viatrexx.com
Inactives: Alcohol 20%, Water 80%

NDC: 63776-484-14
Item: VPC0650
Viatrexx Bio Incorporated
Viatrexx-Sinister 7
Box of 1 X 30 mL spray bottle
For Oral and Topical Use
Expiry date: Lot #:
Manufactured for:
Viatrexx Bio Incorporated Newark, DE, USA, 19713
www.Viatrexx.com
Ingredients, homeopathic
See insert or www.viatrexx.com
Inactives: Alcohol 20%, Water 80%

NDC: 63776-484-15
Item: VPC0650
Viatrexx Bio Incorporated
Viatrexx-Sinister 7
Box of 1 X 50 mL spray bottle
For Oral and Topical Use
Expiry date: Lot #:
Manufactured for:
Viatrexx Bio Incorporated Newark, DE, USA, 19713
www.Viatrexx.com
Ingredients, homeopathic
See insert or www.viatrexx.com
Inactives: Alcohol 20%, Water 80%

NDC: 63776-484-16
Item: VPC0650
Viatrexx Bio Incorporated
Viatrexx-Sinister 7
Box of 1 X 100 mL bottle
For Oral and Topical Use
Expiry date: Lot #:
Manufactured for:
Viatrexx Bio Incorporated Newark, DE, USA, 19713
www.Viatrexx.com
Ingredients, homeopathic
See insert or www.viatrexx.com
Inactives: Alcohol 20%, Water 80%

NDC: 63776-484-17
Item: VPC0650
Viatrexx Bio Incorporated
Viatrexx-Sinister 7
Box of 1 X 250 mL bottle
For Oral and Topical Use
Expiry date: Lot #:
Manufactured for:
Viatrexx Bio Incorporated Newark, DE, USA, 19713
www.Viatrexx.com
Ingredients, homeopathic
See insert or www.viatrexx.com
Inactives: Alcohol 20%, Water 80%